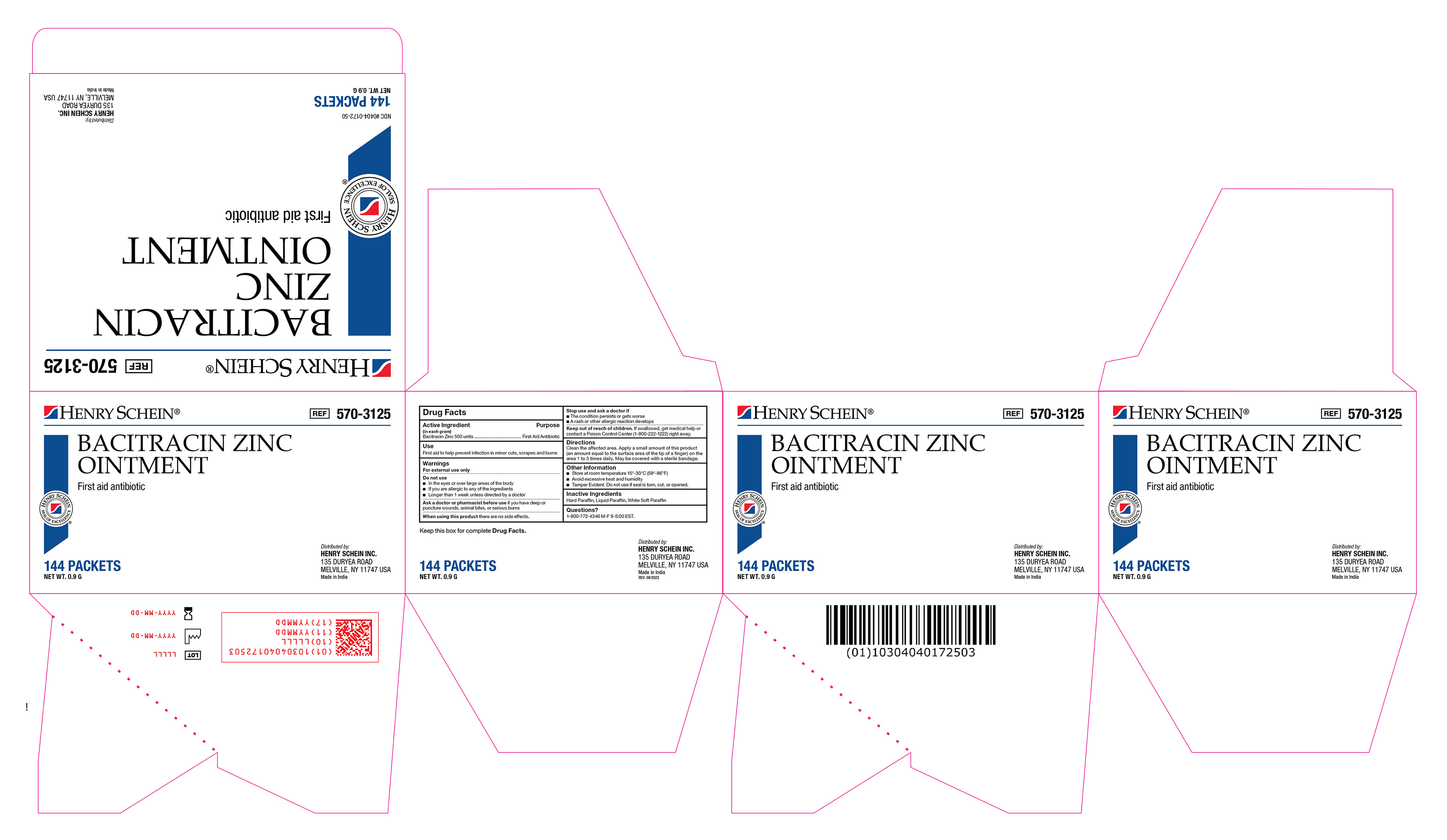 DRUG LABEL: Bacitracin Zinc
NDC: 0404-0172 | Form: OINTMENT
Manufacturer: Henry Schein
Category: otc | Type: HUMAN OTC DRUG LABEL
Date: 20251125

ACTIVE INGREDIENTS: BACITRACIN ZINC 500 [iU]/1 g
INACTIVE INGREDIENTS: MINERAL OIL; PARAFFIN; WHITE PETROLATUM

570-3125 Bacitracin Zinc Ointment NDC 0404-0172-50

Active Ingredient

Bacitracin Zinc (500 units)

Purpose

First Aid Antibiotic

Use(s)

First aid to help prevent infection in minor cuts, scrapes, and burns

Warnings

For External Use Only

Do not use

• In the eyes or over large areas of the body

• If you are allergic to any of the ingredients

• Longer than 1 week unless directed by a doctor

Ask a doctor or pharmacist before use if you have

deep or puncture wounds, animal bites, or serious burns

When using this product

there are no side effects.

Stop use and ask a doctor if

• The condition persists or gets worse

• A rash or other allergic reaction develops

Keep out of reach of children

If swallowed, get medical help or contact a Poison Control Center (1-800-222-1222) right away.

Directions

Clean the affected area. Apply a small amount of this product (an amount equal to the surface area of the tip of a finger) on the area 1 to 3 times daily. May be covered with a sterile bandage.

Other Information

• Store at room temperature 15º-30ºC (59º-86ºF)

• Avoid excessive heat and humidity

• Tamper evident. Do not use if seal is torn, cut, or opened.

Inactive Ingredients

Mineral Oil, Paraffin, White Petrolatum

Questions?

1-888-396-2739 M-F 9-5 EST

Label

Bacitracin Zinc